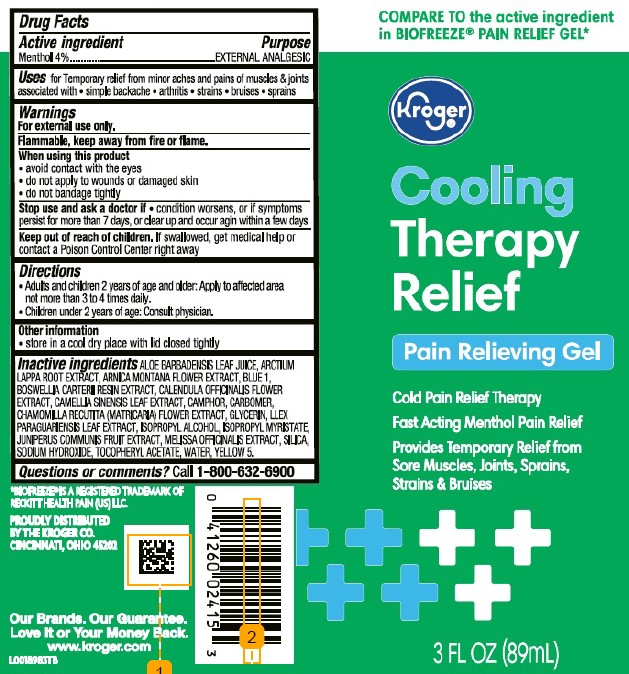 DRUG LABEL: Gel Cooling Pain Relief
NDC: 30142-043 | Form: GEL
Manufacturer: The Kroger Co.
Category: otc | Type: HUMAN OTC DRUG LABEL
Date: 20260227

ACTIVE INGREDIENTS: MENTHOL 40 mg/1 mL
INACTIVE INGREDIENTS: ALOE VERA LEAF; ARCTIUM LAPPA ROOT; ARNICA MONTANA FLOWER; FD&C BLUE NO. 1; FRANKINCENSE; CALENDULA OFFICINALIS FLOWER; GREEN TEA LEAF; CAMPHOR (NATURAL); CARBOMER HOMOPOLYMER, UNSPECIFIED TYPE; CHAMOMILE; GLYCERIN; ILEX PARAGUARIENSIS LEAF; ISOPROPYL ALCOHOL; ISOPROPYL MYRISTATE; JUNIPER BERRY; MELISSA OFFICINALIS WHOLE; SILICON DIOXIDE; SODIUM HYDROXIDE; .ALPHA.-TOCOPHEROL ACETATE; WATER; FD&C YELLOW NO. 5

Kroger 894.002/894AB-AC
Gel Cooling Pain Relief

Active ingredient

Menthol 4%

Purpose

External analgesic

Use

for temporary relief from minor aches and pains of muscles & joints associated with

- simple backache
- arthritis
- strains
- bruises
- sprains

Warnings

For external use only

Flammable, keep away from fire or flame.

When using this product

- avoid contact with the eyes
- do not apply to wounds or damaged skin
- do not bandage tightly

Stop use and ask a doctor if

- condition worsens, or if symptoms persist for more than 7 days or clear up and occur again within a few days

Keep out of reach of children

If swallowed, get medical help or contact a Poison Control Center right away.

Directions

- adults and children 2 years of age and older: apply to affected area not more than 3 to 4 times daily
- children under 2 years of age: consult physician.

Other information

- store in a cool dry place with lid closed tightly

Inactive ingredients

Aloe barbadensis leaf juice, Arctium lappa root extract, Arnica montana flower extract, blue 1, Boswellia carterii resin extract, Calendula officinalis flower extract, Camellia sinensis leaf extract, camphor, carbomer, Chamomilla recutita (matricaria) flower extract, glycerin, llex paraguariensis leaf extract, isopropyl alcohol, isopropyl myristate, Juniperus communis fruit extract, Melissa officinalis extract, silica, sodium hydroxide, tocopheryl acetate, water, yellow 5

Questions or comments?

Call 1-800-632-6900

Disclaimer

*BIOFREEZE®IS A REGISTERED TRADEMARK OF RECKITT HEALTH PAIN (US) LLC.

Adverse Reactions Section

PROUDLY DISTRIBUTED BY THE KROGER CO.

CINCINNATI, OHIO 415202

Our Brands. Our Guarantee. Love It or Your Money Back.

www.kroger.com

principal display panel

COMPARE TO the active ingredient in BIOFREEZE® PAIN RELIEF GEL*

Kroger®

Cooling

Therapy

Relief

Pain Relieving Gel

Cold Pain Relief Therapy

Fast Acting Menthol Pain Relief

Provides Temporary Relief from

Sore Muscles, Joints, Sprains,

Strains & Bruises

3 FL OZ (89 mL)